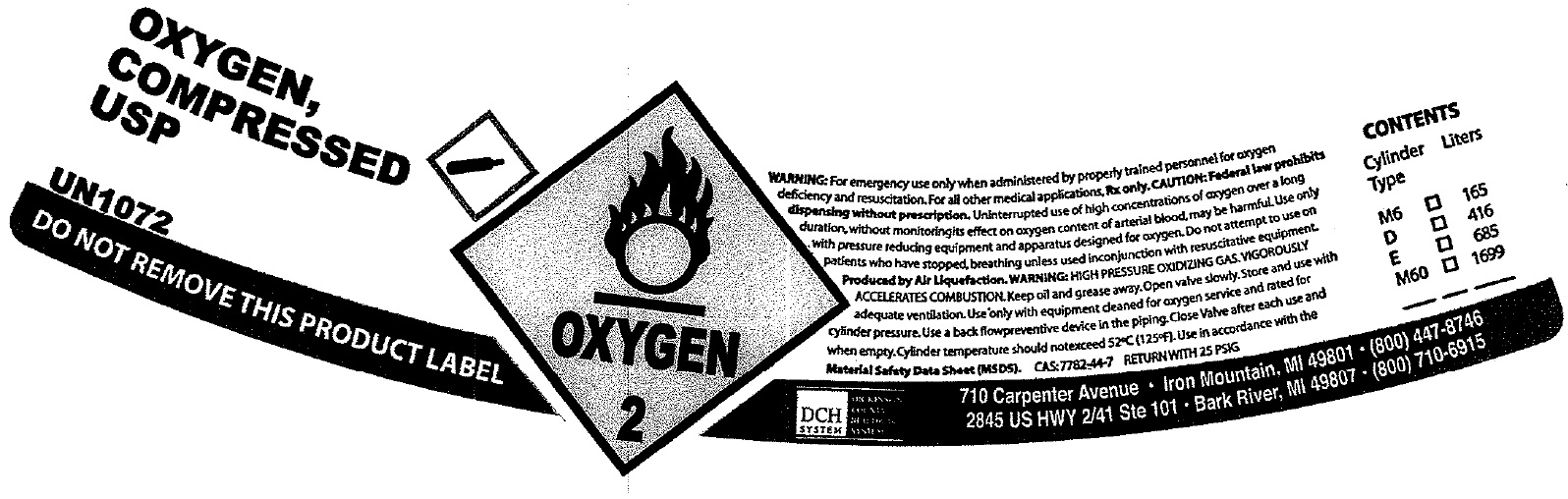 DRUG LABEL: Medical Oxygen Compressed
NDC: 19979-000 | Form: GAS
Manufacturer: MMC - Dickinson Home Medical Equipment
Category: prescription | Type: HUMAN PRESCRIPTION DRUG LABEL
Date: 20240703

ACTIVE INGREDIENTS: OXYGEN 1 L/1 L

Medical Oxygen, Compressed USP

WARNING:

For emergency use only when administered by properly trained personnel for oxygen deficiency and resuscitation. For all other medical applications, Rx only. CAUTION: Federal law prohibits dispensing without prescription. Uninterrupted use of high concentrations of oxygen over a long duration, without monitoring its effect on oxygen content of arterial blood, may be harmful. Use only with pressure reducing equipment and apparatus designed for oxygen. Do not attempt to use on patients who have stopped breathing unless used in conjunction with resuscitative equipment. Prouduced by Air Liquefaction. WARNING: HIGH PRESSURE OXIDIZING GAS VIGOROUSLY ACCELERATES COMBUSTION. Keep oil and grease away. Open valve slowly. Store and use with adequate ventilation.Use only with equipement cleaned for oxygen service and rated for cylinder pressure. Use a back flowpreventive device in the piping. Close Valve after each use and when empty. Cylinder temperature should notexceed 52°C (125°F).Use in accordance with the Material Safety Data Sheet (MS DS).